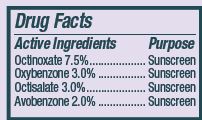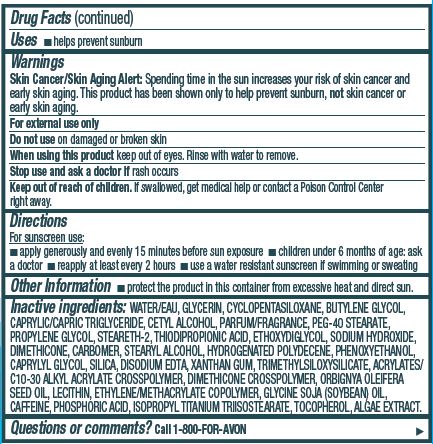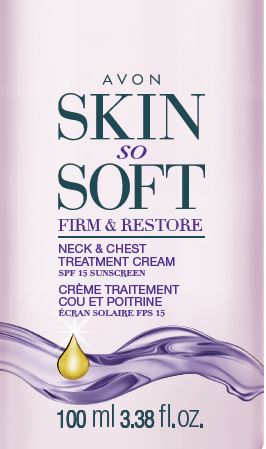 DRUG LABEL: Skin So Soft Firm and Restore
NDC: 10096-0331 | Form: CREAM
Manufacturer: New Avon LLC
Category: otc | Type: HUMAN OTC DRUG LABEL
Date: 20190328

ACTIVE INGREDIENTS: OCTINOXATE	 75 mg/1 mL; OXYBENZONE	 30 mg/1 mL; OCTISALATE	 30 mg/1 mL; AVOBENZONE	 20 mg/1 mL
INACTIVE INGREDIENTS: WATER

Skin So Soft Neck and Chest Cream SPF 15

Active Ingredients
Octinoxate 7.5%......................
Oxybenzone 3.0%...................
Octisalate 3.0%......................
Avobenzone 2.0% ..................

Purpose
................ Sunscreen
................ Sunscreen
................. Sunscreen
.................. Sunscreen

Uses
■ helps prevent sunburn

Warnings
Skin Cancer/Skin Aging Alert: Spending time in the sun increases your risk of skin cancer and early skin aging. This product has been shown only to help prevent sunburn, not skin cancer or early skin aging.

For external use only

Do not use on damaged or broken skin

When using this product keep out of eyes. Rinse with water to remove.

Stop use and ask a doctor if rash occurs

Keep out of reach of children. If swallowed, get medical help or contact a Poison Control Center right away.

Directions

For sunscreen use:
■ apply generously and evenly 15 minutes before sun exposure
■ children under 6 months of age: ask a doctor
■ reapply at least every 2 hours
■ use a water resistant sunscreen if swimming or sweating

Other Information
■ protect the product in this container from excessive heat and direct sun.

INACTIVE INGREDIENT

Inactive ingredients: WATER/EAU, GLYCERIN, CYCLOPENTASILOXANE, BUTYLENE GLYCOL, CAPRYLIC/CAPRIC TRIGLYCERIDE, CETYL ALCOHOL, PARFUM/FRAGRANCE, PEG-40 STEARATE, PROPYLENE GLYCOL, STEARETH-2, THIODIPROPIONIC ACID, ETHOXYDIGLYCOL, SODIUM HYDROXIDE, DIMETHICONE, CARBOMER, STEARYL ALCOHOL, HYDROGENATED POLYDECENE, PHENOXYETHANOL, CAPRYLYL GLYCOL, SILICA, DISODIUM EDTA, XANTHAN GUM, TRIMETHYLSILOXYSILICATE, ACRYLATES/C10-30 ALKYL ACRYLATE CROSSPOLYMER, DIMETHICONE CROSSPOLYMER, ORBIGNYA OLEIFERA SEED OIL, LECITHIN, ETHYLENE/METHACRYLATE COPOLYMER, GLYCINE SOJA (SOYBEAN) OIL, CAFFEINE, PHOSPHORIC ACID, ISOPROPYL TITANIUM TRIISOSTEARATE, TOCOPHEROL, ALGAE EXTRACT.

Questions or comments? Call 1-800-FOR-AVON.